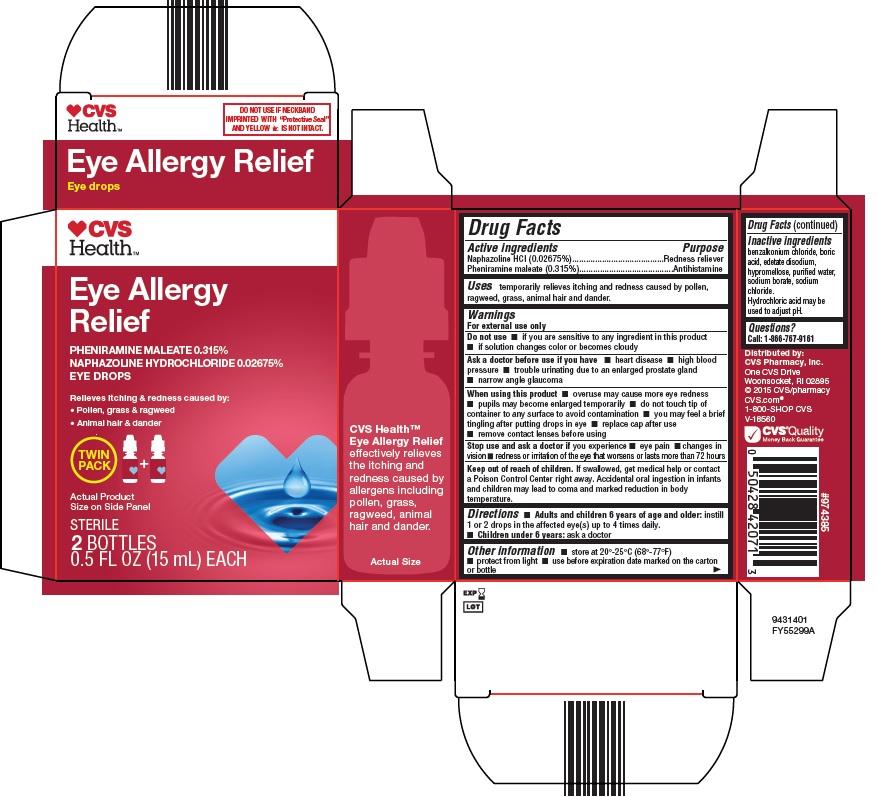 DRUG LABEL: EYE ALLERGY RELIEF
NDC: 69842-441 | Form: SOLUTION/ DROPS
Manufacturer: CVS PHARMACY
Category: otc | Type: HUMAN OTC DRUG LABEL
Date: 20260115

ACTIVE INGREDIENTS: NAPHAZOLINE HYDROCHLORIDE 0.2675 mg/1 mL; PHENIRAMINE MALEATE 3.15 mg/1 mL
INACTIVE INGREDIENTS: BENZALKONIUM CHLORIDE; BORIC ACID; EDETATE DISODIUM; WATER; SODIUM BORATE; SODIUM CHLORIDE; HYDROCHLORIC ACID; HYPROMELLOSE, UNSPECIFIED

Drug Facts

Active Ingredients

Naphazoline HCl (0.02675%)

Pheniramine maleate (0.315%)

Purpose

Redness reliever

Antihistamine

Uses

- temporarily relieves itching and redness caused by pollen, ragweed, grass, animal hair and dander.

Warnings

For external use only

Do not use

- if you are sensitive to any ingredient in this product
- if solution changes color or becomes cloudy

Ask a doctor before use if you have

- heart disease
- high blood pressure
- trouble urinating due to an enlarged prostate gland
- narrow angle glaucoma

When using this product

- overuse may cause more eye redness
- pupils may become enlarged temporarily
- do not touch tip of container to any surface to avoid contamination
- you may feel a brief tingling after putting drops in eye
- replace cap after use
- remove contact lenses before using

Stop use and ask a doctor if you experience

- eye pain
- changes in vision
- redness or irritation of the eye that worsens or lasts more than 72 hours

Keep out of reach of children.

If swallowed, get medical help or contact a Poison Control Center right away. Accidental oral ingestion in infants and children may lead to coma and marked reduction in body temperature.

Directions

- Adults and children 6 years of age and older:instill 1 or 2 drops in the affected eye(s) up to 4 times daily.
- Children under 6 years:ask a doctor

Other information

- store at 20°-25°C (68°-77°F)
- protect from light
- use before expiration date marked on the carton or bottle

Inactive ingredients

benzalkonium chloride, boric acid, edetate disodium, hypromellose, purified water, sodium borate, sodium chloride. Hydrochloric acid may be used to adjust pH.

Questions?

Call: 1-866-767-9161

Package/Label Principal Display Panel

CVS
HealthTM

Eye Allergy Relief
pheniramine maleate 0.315%
Naphazoline hydrochloride 0.02675%
EYE DROPS

Relieves itching & redness caused by :

- Pollen, grass & ragweed
- Animal hair & dander

TWIN
PACK

[two bottle icon]
[teardrop icon]

Actual Product
Size on Side Panel
STERILE
2 BOTTLES
0.5 FL OZ (15 ml) EACH